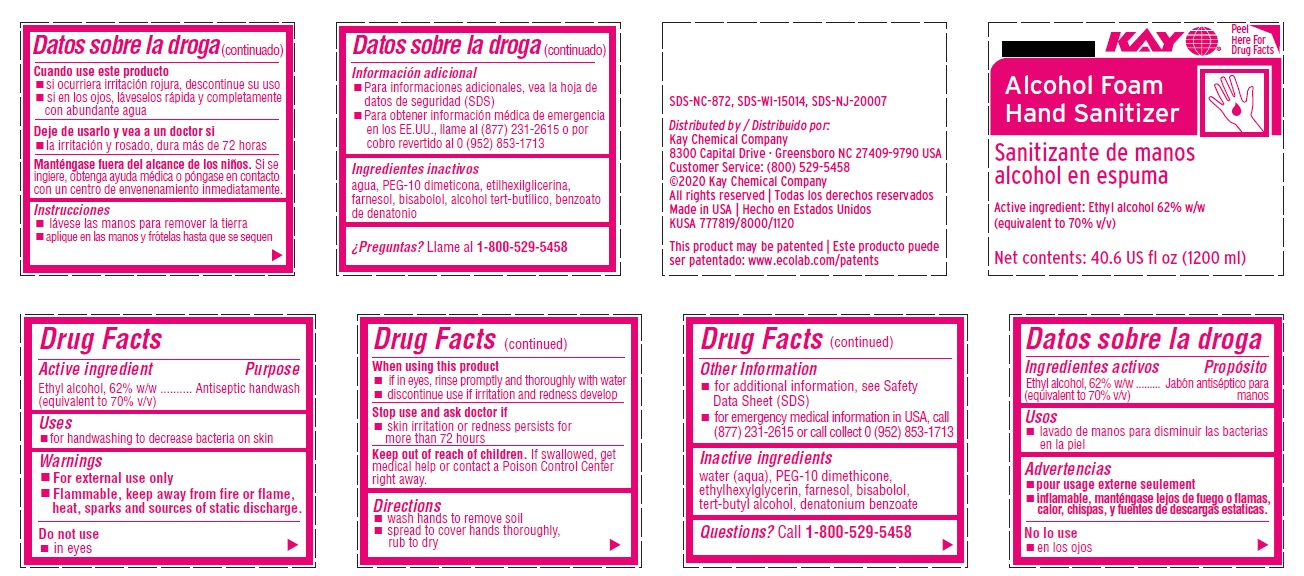 DRUG LABEL: Kay Alcohol Foam Hand Sanitizer
NDC: 47593-686 | Form: SOLUTION
Manufacturer: Ecolab Inc.
Category: otc | Type: HUMAN OTC DRUG LABEL
Date: 20251231

ACTIVE INGREDIENTS: ALCOHOL 70 mL/100 mL
INACTIVE INGREDIENTS: WATER; BIS-PEG-12 DIMETHICONE (500 MPA.S); ETHYLHEXYLGLYCERIN; FARNESOL; .ALPHA.-BISABOLOL, (+/-)-; TERT-BUTYL ALCOHOL; DENATONIUM BENZOATE

Drug Facts

Active ingredient

Ethyl alcohol, 62% w/w (equivalent to 70% v/v)

Purpose

Antiseptic handwash

Uses

- for hand washing to decrease bacteria on the skin

Warnings

- For external use only
- FLAMMABLE, keep away from fire or flame, heat, sparks and sources of static discharge.

Do not use

- in eyes

When using this product

- if in eyes, rinse promptly and throughly with water
- discontinue use if irritation and redness develop

Stop use and ask doctor if skin irritation and redness persists from more than 72 hours

Keep out of reach of children. If swallowed, get medical help or contact a Poison Control Center right away.

Directions

- wash hands to remove soil
- spread to cover hands thoroughly, rub to dry

Other information

- for additional information, see Safety Data Sheet (SDS)
- for emergency medical information in USA, call (877) 231-2615 or call collect - 0 (952) 853-1713

INACTIVE INGREDIENT

Inactive ingredients water (aqua), PEG-10 dimethicone, ethylhexylglycerin, farnesol, bisabolol, tert-butyl alcohol, denatonium benzoate

Questions? call 1-800-529-5458

Principal display panel and representative label

KAY

Alcohol Foam

Hand Sanitizer

Active ingredient: Ethyl alcohol 62% w/w (equivalent to 70% v/v)

Net contents: 40.6 US fl oz (1200 mL)

SDS-NC-872, SDS-WI-15014, SDS-NJ-20007

Distributed by

Kay Chemical Company

8300 Capital Drive - Greensboro NC 27409-9790 USA

Customer Service: (800) 529-5458

(c)2020 Kay Chemical Company

All rights reserved

Made in USA